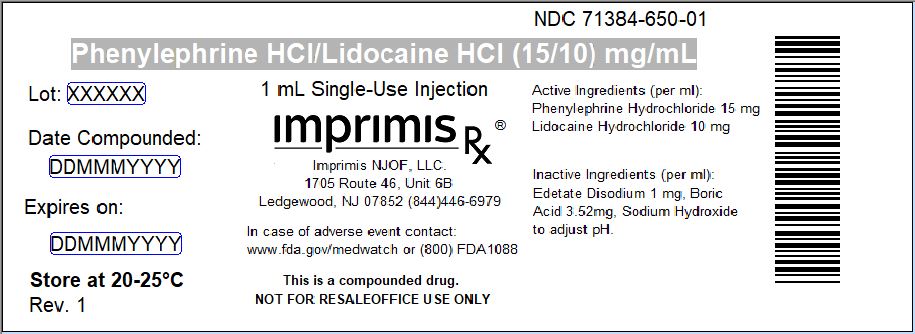 DRUG LABEL: Phenyl-Lido
NDC: 71384-650 | Form: INJECTION, SOLUTION
Manufacturer: Imprimis NJOF, LLC
Category: prescription | Type: HUMAN PRESCRIPTION DRUG LABEL
Date: 20200212

ACTIVE INGREDIENTS: LIDOCAINE HYDROCHLORIDE 10 mg/1 mL; PHENYLEPHRINE HYDROCHLORIDE 15 mg/1 mL

STORAGE AND HANDLING

Store at 20° to 25° C (68° to 77° F)